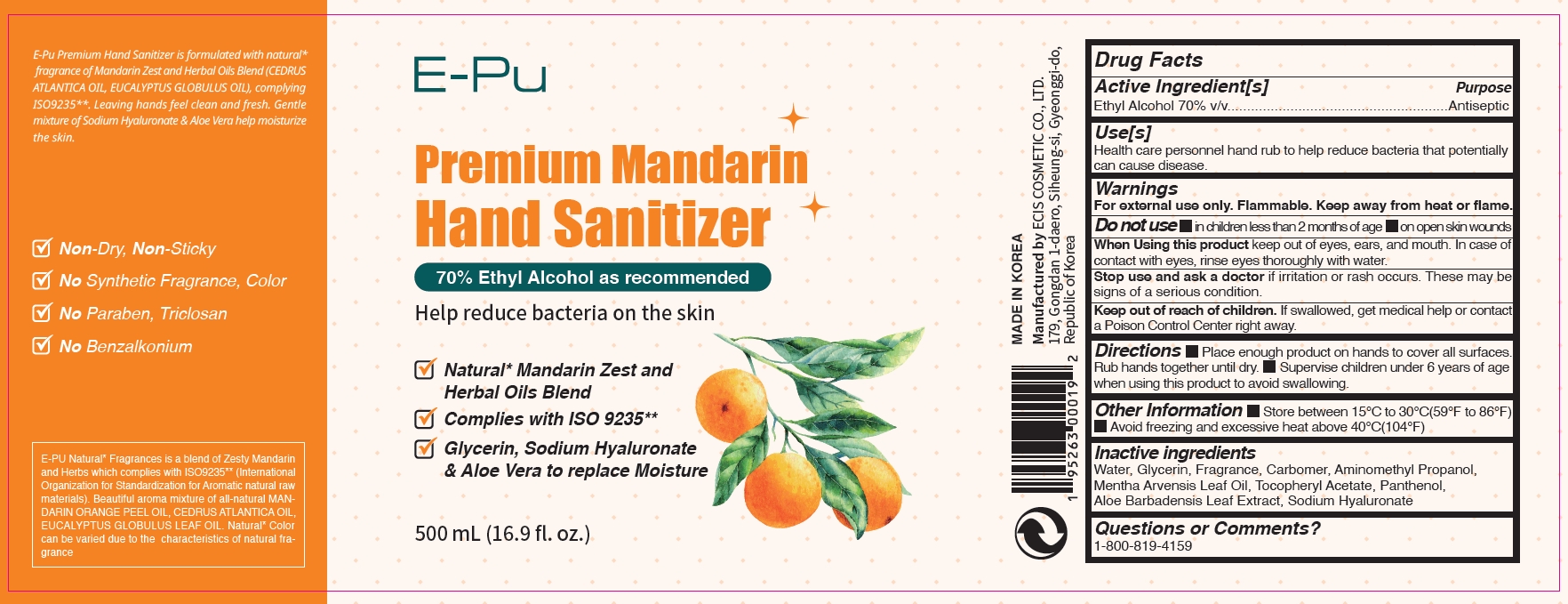 DRUG LABEL: EPu Premium Mandarin Hand Sanitizer 70 500ml
NDC: 73862-209 | Form: GEL
Manufacturer: E.CIS Cosmetic Co.,Ltd
Category: otc | Type: HUMAN OTC DRUG LABEL
Date: 20200608

ACTIVE INGREDIENTS: ALCOHOL 70 mL/100 mL
INACTIVE INGREDIENTS: AMINOMETHYLPROPANOL; ALOE VERA LEAF; MENTHA ARVENSIS LEAF OIL; PANTHENOL; HYALURONATE SODIUM; GLYCERIN; WATER; CARBOMER 940; .ALPHA.-TOCOPHEROL ACETATE

EPu Premium Mandarin Hand Sanitizer 70% 500ml

Active Ingredient(s)

Alcohol 70% v/v. Purpose: Antiseptic

Purpose

Antiseptic, Hand Sanitizer

Use

Health care personnel hand rub to help reduce bacterial that potentially can cause disease.

Warnings

For external use only. Flammable. Keep away from heat or flame

Do not use

- in children less than 2 months of age
- on open skin wounds

When using this product keep out of eyes, ears, and mouth. In case of contact with eyes, rinse eyes thoroughly with water.

Stop use and ask a doctor if irritation or rash occurs. These may be signs of a serious condition.

Keep out of reach of children. If swallowed, get medical help or contact a Poison Control Center right away.

Directions

- Place enough product on hands to cover all surfaces. Rub hands together until dry.
- Supervise children under 6 years of age when using this product to avoid swallowing.

Other information

- Store between 15℃ to 30℃ (59℉ to 86℉)
- Avoid freezing and excessive heat above 40℃ (104℉)

Inactive ingredients

Water, Glycerin, Fragrance, Carbomer, Aminomethyl Propanol, Mentha Arvensis Leaf Oil, Tocopheryl Acetate, Panthenol, Aloe Barbadensis Leaf Extract, Sodium Hyaluronate

Package Label - Principal Display Panel

E-Pu

Premium Mandarin

Hand Sanitizer

70% Ethyl Alcohol as recommended

Help reduce bacteria on the skin

- Natural* Mandarin Zest and Herbal Oils Blend
- Complies with ISO 9235**
- Glycerin, Sodium Hyaluronate & Aloe Vera to replace Moisture

500mL (16.9 fl.oz.)